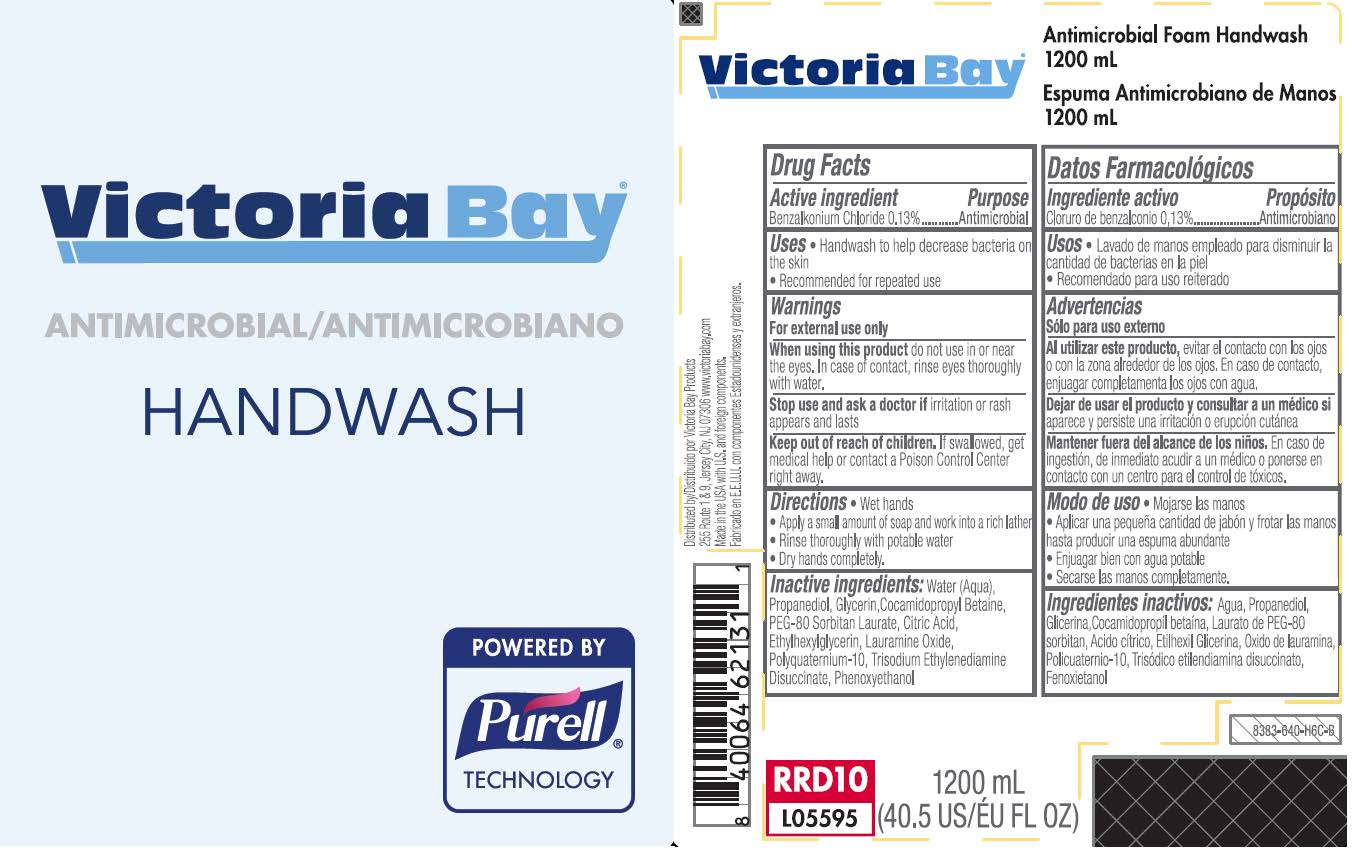 DRUG LABEL: Victoria Bay Antimicrobial Foam Handwash 1200 mL
NDC: 71907-114 | Form: LIQUID
Manufacturer: Dade Paper & Bag, LLC
Category: otc | Type: HUMAN OTC DRUG LABEL
Date: 20250109

ACTIVE INGREDIENTS: BENZALKONIUM CHLORIDE 0.0013 mg/1 mL
INACTIVE INGREDIENTS: WATER; PROPANEDIOL; GLYCERIN; COCAMIDOPROPYL BETAINE; PEG-80 SORBITAN LAURATE; CITRIC ACID MONOHYDRATE; ETHYLHEXYLGLYCERIN; LAURAMINE OXIDE; POLYQUATERNIUM-10 (10000 MPA.S AT 2%); TRISODIUM ETHYLENEDIAMINE DISUCCINATE; PHENOXYETHANOL

Victoria Bay® Antimicrobial Foam Handwash 1200 mL

Active ingredient

Benzalkonium Chloride 0.13%

Purpose

Antimicrobial

Uses

• Handwash to help decrease bacteria on the skin

• Recommended for repeated use

Warnings

For external use only

WHEN USING

When using this productdo not use in or near the eyes. In case of contact, rinse eyes thoroughly with water.

Stop use and ask a doctorif irritation or rash appears and lasts

Keep out of reach of children.If swallowed, get medical help or contact a Poison Control Center right away.

Directions

• Wet hands

• Apply a small amount of soap and work into a rich lather

• Rinse thoroughly with potable water

• Dry hands completely

Inactive Ingredients

Water (Aqua), Propanediol, Glycerin, Cocamidopropyl Betaine, PEG-80 Sorbitan Laurate, Citric Acid, Ethylhexylglycerin, Lauramine Oxide, Polyquaternium-10, Trisodium Ethylenediamine Disuccinate, Phenoxyethanol